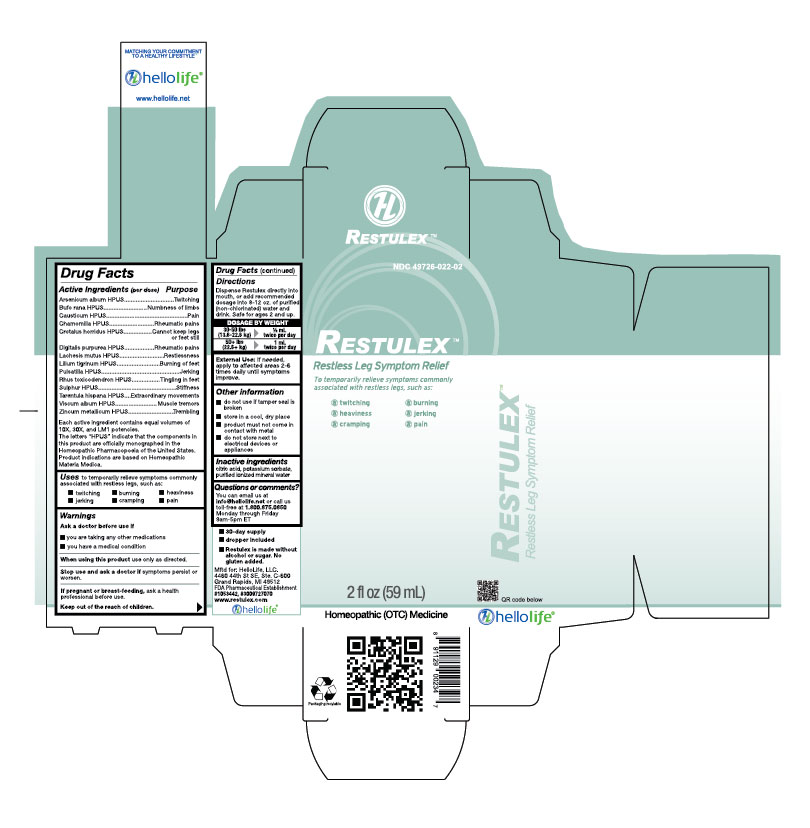 DRUG LABEL: Restulex
NDC: 49726-022 | Form: LIQUID
Manufacturer: Hello Life, Inc.
Category: homeopathic | Type: HUMAN OTC DRUG LABEL
Date: 20181226

ACTIVE INGREDIENTS: ARSENIC TRIOXIDE 10 [hp_X]/59 mL; BUFO BUFO CUTANEOUS GLAND 10 [hp_X]/59 mL; CAUSTICUM 10 [hp_X]/59 mL; MATRICARIA RECUTITA 10 [hp_X]/59 mL; CROTALUS HORRIDUS HORRIDUS VENOM 10 [hp_X]/59 mL; DIGITALIS 10 [hp_X]/59 mL; LACHESIS MUTA VENOM 10 [hp_X]/59 mL; LILIUM LANCIFOLIUM FLOWERING TOP 10 [hp_X]/59 mL; PULSATILLA VULGARIS 10 [hp_X]/59 mL; TOXICODENDRON PUBESCENS LEAF 10 [hp_X]/59 mL; SULFUR 10 [hp_X]/59 mL; LYCOSA TARANTULA 10 [hp_X]/59 mL; VISCUM ALBUM FRUITING TOP 10 [hp_X]/59 mL; ZINC 10 [hp_X]/59 mL
INACTIVE INGREDIENTS: WATER; CITRIC ACID MONOHYDRATE; POTASSIUM SORBATE

Drug Facts

Active Ingredients (per dose)

Arsenicum album HPUS
Bufo rana HPUS
Causticum HPUS
Chamomilla HPUS
Crotalus horridus HPUS
Digitalis purpurea HPUS
Lachesis mutus HPUS
Lilium tigrinum HPUS
Pulsatilla HPUS
Rhus toxicodendron HPUS
Sulphur HPUS
Tarentula hispana HPUS
Viscum album HPUS
Zincum metallicum HPUS
Each active ingredient contains equal volumes of 10X, 30X, and LM1 potencies. The letters “HPUS” indicate that the components in this product are officially monographed in the Homeopathic Pharmacopoeia of the United States. Product indications are based on Homeopathic Materia Medica.

Purpose

Arsenicum album HPUS..............................Twitching
Bufo rana HPUS...........................................Numbness of limbs
Causticum HPUS..........................................Pain
Chamomilla HPUS.......................................Rheumatic pains
Crotalus horridus HPUS..............................Cannot keep legs or feet still
Digitalis purpurea HPUS..............................Rheumatic pains
Lachesis mutus HPUS..................................Restlessness
Lilium tigrinum HPUS..................................Burning of feet
Pulsatilla HPUS............................................Jerking
Rhus toxicodendron HPUS..........................Tingling in feet
Sulphur HPUS..............................................Stiffness
Tarentula hispana HPUS..............................Extraordinary movements
Viscum album HPUS....................................Muscle tremors
Zincum metallicum HPUS............................Trembling

Uses

to temporarily relieve symptoms commonly associated with restless legs, such as:
• twitching
• jerking
• burning
• cramping
• heaviness
• pain

Warnings

Ask a doctor before use if

- you are taking any other medications
- you have a medical condition

When using this product, use only as directed.

Stop use and ask a doctor if symptoms persist or worsen.

PREGNANCY OR BREAST FEEDING

If pregnant or breast-feeding, ask a health professional before use.

Keep out of the reach of children.

Directions

Dispense Restulex directly into mouth, or add recommended dosage into 8-12 oz of purified (non-chlorinated) water and drink. Safe for ages 2 and up.

DOSAGE BY WEIGHT

30-50 lbs (13.6-22.6 kg) 1/2 mL twice per day

50+ lbs (22.6+ kg) 1 mL twice per day

External Use: If needed, apply to affected areas 2-6 times daily until symptoms improve.

Other information

- do not use if tamper seal is broken
- store in a cool, dry place
- product must not come in contact with metal
- do not store next to electrical devices or appliances

Inactive ingredients

citric acid, potassium sorbate, purified ionized mineral water

Questions or comments?

You can email us at info@hellolife.net or call us toll-free at 1.800.875.0850 Monday through Friday 9am-5pm ET

DESCRIPTION

- 30-day supply
- dropper included
- Restulex is made without alcohol or sugar. No gluten added.

Mftd for: HelloLife, LLC.
4460 44th St SE, Ste. C-600
Grand Rapids, MI 49512
FDA Pharmaceutical Establishment
#1053442, #3009727070
www.restulex.com

Principal Display Panel:

NDC 49726-022-02
RESTULEXTM
Restless Leg Symptom Relief
To temporarily relieve symptoms commonly associated with restless legs, such as:
• twitching
• burning
• heaviness
• jerking
• cramping
• pain
2 fl oz (59 mL)
Homeopathic (OTC) Medicine